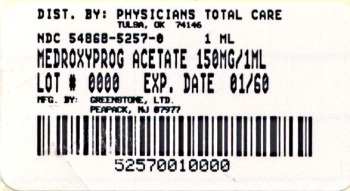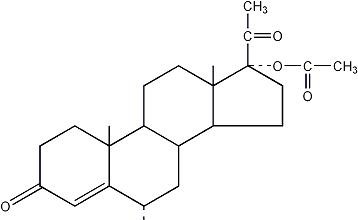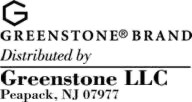 DRUG LABEL: MEDROXYPROGESTERONE ACETATE
NDC: 54868-5257 | Form: INJECTION, SUSPENSION
Manufacturer: Physicians Total Care, Inc.
Category: prescription | Type: HUMAN PRESCRIPTION DRUG LABEL
Date: 20090813

ACTIVE INGREDIENTS: MEDROXYPROGESTERONE ACETATE 150 mg/1 mL
INACTIVE INGREDIENTS: POLYETHYLENE GLYCOL 3350 28.9 mg/1 mL; POLYSORBATE 80 2.41 mg/1 mL; SODIUM CHLORIDE 8.68 mg/1 mL; METHYLPARABEN 1.37 mg/1 mL; PROPYLPARABEN 0.15 mg/1 mL; WATER; SODIUM HYDROXIDE; HYDROCHLORIC ACID

Medroxyprogesterone Acetate Injectable Suspension, USP

BOXED WARNING

Women who use Medroxyprogesterone Acetate Injectable Suspension, USP may lose significant bone mineral density. Bone loss is greater with increasing duration of use and may not be completely reversible.

It is unknown if use of Medroxyprogesterone Acetate Injectable Suspension, USP during adolescence or early adulthood, a critical period of bone accretion, will reduce peak bone mass and increase the risk for osteoporotic fracture in later life.

Medroxyprogesterone Acetate Injectable Suspension, USP should be used as a long-term birth control method (e.g. longer than 2 years) only if other birth control methods are inadequate. (See WARNINGS.)

Patients should be counseled that this product does not protect against HIV infection (AIDS) and other sexually transmitted diseases.

DESCRIPTION

Medroxyprogesterone Acetate Injectable Suspension, USP contains medroxyprogesterone acetate, a derivative of progesterone, as its active ingredient. Medroxyprogesterone Acetate is active by the parenteral and oral routes of administration. It is a white to off-white; odorless crystalline powder that is stable in air and that melts between 200°C and 210°C. It is freely soluble in chloroform, soluble in acetone and dioxane, sparingly soluble in alcohol and methanol, slightly soluble in ether, and insoluble in water.

The chemical name for Medroxyprogesterone Acetate is pregn-4-ene-3,20-dione, 17-(acetyloxy)-6-methyl-, (6α-).

The structural formula is as follows:

medroxyprogesterone acetate

Medroxyprogesterone Acetate Injectable Suspension, USP for intramuscular (IM) injection is available in vials and prefilled syringes, each containing 1 mL of Medroxyprogesterone Acetate sterile aqueous suspension 150 mg/mL.
Each mL contains:

Medroxyprogesterone acetate | 150 mg
Polyethylene glycol 3350 | 28.9 mg
Polysorbate 80 | 2.41 mg
Sodium chloride | 8.68 mg
Methylparaben | 1.37 mg
Propylparaben | 0.150 mg
Water for injection | qs

When necessary, pH is adjusted with sodium hydroxide or hydrochloric acid, or both.

CLINICAL PHARMACOLOGY

Medroxyprogesterone Acetate Injectable Suspension, USP, when administered at the recommended dose to women every 3 months, inhibits the secretion of gonadotropins which, in turn, prevents follicular maturation and ovulation and results in endometrial thinning. These actions produce its contraceptive effect.

Following a single 150 mg IM dose of Medroxyprogesterone Acetate Injectable Suspension, USP, Medroxyprogesterone Acetate concentrations, measured by an extracted radioimmunoassay procedure, increase for approximately 3 weeks to reach peak plasma concentrations of 1 to 7 ng/mL. The levels then decrease exponentially until they become undetectable (<100 pg/mL) between 120 to 200 days following injection. Using an unextracted radioimmunoassay procedure for the assay of Medroxyprogesterone Acetate in serum, the apparent half-life for Medroxyprogesterone Acetate following IM administration of Medroxyprogesterone Acetate Injectable Suspension, USP is approximately 50 days.

Women with lower body weights conceive sooner than women with higher body weights after discontinuing Medroxyprogesterone Acetate Injectable Suspension, USP.

The effect of hepatic and/or renal disease on the pharmacokinetics of Medroxyprogesterone Acetate Injectable Suspension, USP is unknown.

INDICATIONS AND USAGE

Medroxyprogesterone Acetate Injectable Suspension, USP is indicated only for the prevention of pregnancy. The loss of bone mineral density (BMD) in women of all ages and the impact on peak bone mass in adolescents should be considered, along with the decrease in BMD that occurs during pregnancy and/or lactation, in the risk/benefit assessment for women who use Medroxyprogesterone Acetate Injectable Suspension, USP long-term (see WARNINGS.) It is a long-term injectable contraceptive in women when administered at 3-month (13-week) intervals. Dosage does not need to be adjusted for body weight.

In five clinical studies using Medroxyprogesterone Acetate Injectable Suspension, USP, the 12-month failure rate for the group of women treated with Medroxyprogesterone Acetate Injectable Suspension, USP was zero (no pregnancies reported) to 0.7 by Life-Table method. Pregnancy rates with contraceptive measures are typically reported for only the first year of use as shown in Table 1. Except for intrauterine devices (IUD), implants, sterilization, and Medroxyprogesterone Acetate Injectable Suspension, USP, the efficacy of these contraceptive measures depends in part on the reliability of use. The effectiveness of Medroxyprogesterone Acetate Injectable Suspension, USP is dependent on the patient returning every 3 months (13 weeks) for reinjection.

Table 1 Lowest Expected and Typical Failure Rates [Lowest expected - when used exactly as directed. Typical - includes those not following directions exactly.] Expressed as Percent of Women Experiencing an Accidental Pregnancy in the First Year of Continuous Use
Method | Lowest Expected | Typical
Injectable progestogen
Medroxyprogesterone | 0.3 | 0.3
Acetate
Implants
Norplant (6 capsules) | 0.2 [from Norplant® package insert.] | 0.2
Female sterilization | 0.2 | 0.4
Male sterilization | 0.1 | 0.15
Pill |  | 3
Combined | 0.1
Progestogen only | 0.5
IUD |  | 3
Progestasert | 2
Copper T 380A | 0.8
Condom | 2 | 12
Diaphragm | 6 | 18
Cap | 6 | 18
Spermicides | 3 | 21
Sponge
Parous women | 9 | 28
Nulliparous women | 6 | 18
Periodic abstinence | 1–9 | 20
Withdrawal | 4 | 18
No method | 85 | 85
Source: Trussell et al^1

CONTRAINDICATIONS

1. Known or suspected pregnancy or as a diagnostic test for pregnancy.
2. Undiagnosed vaginal bleeding.
3. Known or suspected malignancy of breast.
4. Active thrombophlebitis, or current or past history of thromboembolic disorders, or cerebral vascular disease.
5. Significant liver disease.
6. Known hypersensitivity to Medroxyprogesterone Acetate Injectable Suspension, USP (Medroxyprogesterone Acetate or any of its other ingredients).

WARNINGS

1. Loss of Bone Mineral Density

Use of Medroxyprogesterone Acetate Injectable Suspension, USP reduces serum estrogen levels and is associated with significant loss of bone mineral density (BMD) as bone metabolism accommodates to a lower estrogen level. This loss of BMD is of particular concern during adolescence and early adulthood, a critical period of bone accretion. It is unknown if use of Medroxyprogesterone Acetate Injectable Suspension, USP by younger women will reduce peak bone mass and increase the risk for osteoporotic fracture in later life. In both adults and adolescents, the decrease in BMD appears to be at least partially reversible after Medroxyprogesterone Acetate Injectable Suspension, USP is discontinued and ovarian estrogen production increases. A study to assess the reversibility of loss of BMD in adolescents is ongoing.

Medroxyprogesterone Acetate Injectable Suspension, USP should be used as a long-term birth control method (e.g. longer than 2 years) only if other birth control methods are inadequate. BMD should be evaluated when a woman needs to continue to use Medroxyprogesterone Acetate Injectable Suspension, USP long term. In adolescents, interpretation of BMD results should take into account patient age and skeletal maturity.

Other birth control methods should be considered in the risk/benefit analysis for the use of Medroxyprogesterone Acetate Injectable Suspension, USP in women with osteoporosis risk factors. Medroxyprogesterone Acetate Injectable Suspension, USP can pose an additional risk in patients with risk factors for osteoporosis (e.g., metabolic bone disease, chronic alcohol and/or tobacco use, anorexia nervosa, strong family history of osteoporosis or chronic use of drugs that can reduce bone mass such as anticonvulsants or corticosteroids). Although there are no studies addressing whether calcium and Vitamin D may lessen BMD loss in women using Medroxyprogesterone Acetate Injectable Suspension, USP, all patients should have adequate calcium and Vitamin D intake.

BMD Changes in Adult Women

In a controlled, clinical study, adult women using Medroxyprogesterone Acetate Injectable Suspension, USP for up to 5 years showed spine and hip BMD mean decreases of 5–6%, compared to no significant change in BMD in the control group. The decline in BMD was more pronounced during the first two years of use, with smaller declines in subsequent years. Mean changes in lumbar spine BMD of -2.86%, -4.11%, -4.89%, -4.93% and -5.38% after 1, 2, 3, 4, and 5 years, respectively, were observed. Mean decreases in BMD of the total hip and femoral neck were similar.

After stopping use of Medroxyprogesterone Acetate Injectable Suspension, USP (150 mg), there was partial recovery of BMD toward baseline values during the 2-year post-therapy period. Longer duration of treatment was associated with less complete recovery during this 2-year period following the last injection. Table 2 shows the extent of recovery of BMD for women who completed 5 years of treatment.

Table 2. Mean Percent Change from Baseline in BMD in Adults by Skeletal Site and Cohort
Time in Study | Spine |  | Total Hip |  | Femoral Neck
Time in Study | Medroxy-progesterone Acetate [The treatment group consisted of women who received Medroxyprogesterone Acetate Injectable Suspension, USP for 5 years and were then followed for 2 years post-use.] | Control [The control group consisted of women who did not use hormonal contraception and were followed for 7 years.] | Medroxy-progesterone Acetate | Control | Medroxy-progesterone Acetate | Control
5 years | n=33 | n=105 | n=21 | n=65 | n=34 | n=106
 | -5.38% | 0.43% | -5.16% | 0.19% | -6.12% | -0.27%
7 years | n=12 | n=60 | n=7 | n=39 | n=13 | n=63
 | -3.13% | 0.53% | -1.34% | 0.94% | -5.38% | -0.11%

BMD Changes in Adolescent Females (12–18 years of age)

Preliminary results from an ongoing, open-label, self-selected, non-randomized clinical study of adolescent females (12–18 years) also showed that Medroxyprogesterone Acetate Injectable Suspension, USP use was associated with a significant decline in BMD from baseline (Table 3). In general, adolescents increase bone density during the period of growth following menarche, as seen in the untreated cohort. However, the two cohorts were not matched at baseline for age, gynecologic age, race, BMD and other factors that influence the rate of acquisition of bone mineral density, with the result that they differed with respect to these demographic factors.

Preliminary data from the small number of adolescents participating in the 2-year post-use observation period demonstrated partial recovery of BMD.

Table 3. Mean Percent Change from Baseline in BMD in Adolescents by Skeletal Site and Cohort
Duration of Treatment | Medroxyprogesterone Acetate Injectable Suspension, USP (150 mg IM) |  | Unmatched, Untreated Cohort
 | N | Mean % Change | N | Mean % Change
Total Hip BMD
Week 60 (1.2 years) | 103 | -2.82 | 171 | 1.32
Week 144 (2.8 years) | 45 | -6.16 | 111 | 1.74
Week 240 (4.6 years) | 9 | -6.92 | 69 | 1.12
Femoral Neck BMD
Week 60 | 103 | -3.05 | 171 | 1.87
Week 144 | 45 | -6.01 | 111 | 2.54
Week 240 | 9 | -6.06 | 69 | 1.45
Lumbar Spine BMD
Week 60 | 104 | -2.42 | 171 | 3.47
Week 144 | 46 | -2.78 | 111 | 5.41
Week 240 | 9 | -4.17 | 70 | 5.12

2. Bleeding Irregularities

Most women using Medroxyprogesterone Acetate Injectable Suspension, USP experience disruption of menstrual bleeding patterns. Altered menstrual bleeding patterns include irregular or unpredictable bleeding or spotting, or rarely, heavy or continuous bleeding. If abnormal bleeding persists or is severe, appropriate investigation should be instituted to rule out the possibility of organic pathology, and appropriate treatment should be instituted when necessary.

As women continue using Medroxyprogesterone Acetate Injectable Suspension, USP, fewer experience irregular bleeding and more experience amenorrhea. By month 12 amenorrhea was reported by 55% of women, and by month 24 amenorrhea was reported by 68% of women using Medroxyprogesterone Acetate Injectable Suspension, USP.^2

3. Cancer Risks

Long-term case-controlled surveillance of users of Medroxyprogesterone Acetate Injectable Suspension, USP found slight or no increased overall risk of breast cancer^3 and no overall increased risk of ovarian,^4 liver,^5 or cervical^6 cancer and a prolonged, protective effect of reducing the risk of endometrial^7 cancer in the population of users.

A pooled analysis^14 from two case-control studies, the World Health Organization Study^3 and the New Zealand Study^13, reported the relative risk (RR) of breast cancer for women who had ever used Medroxyprogesterone Acetate Injectable Suspension, USP as 1.1 (95% confidence interval (CI) 0.97 to 1.4). Overall, there was no increase in risk with increasing duration of use of Medroxyprogesterone Acetate Injectable Suspension, USP. The RR of breast cancer for women of all ages who had initiated use of Medroxyprogesterone Acetate Injectable Suspension, USP within the previous 5 years was estimated to be 2.0 (95% CI 1.5 to 2.8).

The World Health Organization Study^3, a component of the pooled analysis^14 described above, showed an increased RR of 2.19 (95% CI 1.23 to 3.89) of breast cancer associated with use of Medroxyprogesterone Acetate Injectable Suspension, USP in women whose first exposure to drug was within the previous 4 years and who were under 35 years of age. However, the overall RR for ever-users of Medroxyprogesterone Acetate Injectable Suspension, USP was only 1.2 (95% CI 0.96 to 1.52).

[NOTE: A RR of 1.0 indicates neither an increased nor a decreased risk of cancer associated with the use of the drug, relative to no use of the drug. In the case of the subpopulation with a RR of 2.19, the 95% CI is fairly wide and does not include the value of 1.0, thus inferring an increased risk of breast cancer in the defined subgroup relative to nonusers. The value of 2.19 means that women whose first exposure to drug was within the previous 4 years and who are under 35 years of age have a 2.19 fold (95% CI 1.23 to 3.89-fold) increased risk of breast cancer relative to nonusers. The National Cancer Institute^8 reports an average annual incidence rate for breast cancer for US women, all races, age 30 to 34 years of 26.7 per 100,000. A RR of 2.19, thus, increases the possible risk from 26.7 to 58.5 cases per 100,000 women. The attributable risk, thus, is 31.8 per 100,000 women per year.]

A statistically insignificant increase in RR estimates of invasive squamous-cell cervical cancer has been associated with the use of Medroxyprogesterone Acetate Injectable Suspension, USP in women who were first exposed before the age of 35 years (RR 1.22 to 1.28 and 95% CI 0.93 to 1.70). The overall, nonsignificant relative rate of invasive squamous-cell cervical cancer in women who ever used Medroxyprogesterone Acetate Injectable Suspension, USP was estimated to be 1.11 (95% CI 0.96 to 1.29). No trends in risk with duration of use or times since initial or most recent exposure were observed.

4. Thromboembolic Disorders

The physician should be alert to the earliest manifestations of thrombotic disorders (thrombophlebitis, pulmonary embolism, cerebrovascular disorders, and retinal thrombosis). Should any of these occur or be suspected, the drug should not be readministered.

5. Ocular Disorders

Medication should not be readministered pending examination if there is a sudden partial or complete loss of vision or if there is a sudden onset of proptosis, diplopia, or migraine. If examination reveals papilledema or retinal vascular lesions, medication should not be readministered.

6. Unexpected Pregnancies

To ensure that Medroxyprogesterone Acetate Injectable Suspension, USP is not administered inadvertently to a pregnant woman, the first injection must be given ONLY during the first 5 days of a normal menstrual period; ONLY within the first 5-days postpartum if not breast-feeding, and if exclusively breast-feeding, ONLY at the sixth postpartum week (see DOSAGE AND ADMINISTRATION).

Neonates from unexpected pregnancies that occur 1 to 2 months after injection of Medroxyprogesterone Acetate Injectable Suspension, USP may be at an increased risk of low birth weight, which, in turn, is associated with an increased risk of neonatal death. The attributable risk is low because such pregnancies are uncommon.^9,10

A significant increase in incidence of polysyndactyly and chromosomal anomalies was observed among infants of users of Medroxyprogesterone Acetate Injectable Suspension, USP, the former being most pronounced in women under 30 years of age. The unrelated nature of these defects, the lack of confirmation from other studies, the distant preconceptual exposure to Medroxyprogesterone Acetate Injectable Suspension, USP, and the chance effects due to multiple statistical comparisons, make a causal association unlikely.^11

Neonates exposed to Medroxyprogesterone Acetate in utero and followed to adolescence, showed no evidence of any adverse effects on their health including their physical, intellectual, sexual, or social development.

Several reports suggest an association between intrauterine exposure to progestational drugs in the first trimester of pregnancy and genital abnormalities in male and female fetuses. The risk of hypospadias (five to eight per 1,000 male births in the general population) may be approximately doubled with exposure to these drugs. There are insufficient data to quantify the risk to exposed female fetuses, but because some of these drugs induce mild virilization of the external genitalia of the female fetus and because of the increased association of hypospadias in the male fetus, it is prudent to avoid the use of these drugs during the first trimester of pregnancy.

To ensure that Medroxyprogesterone Acetate Injectable Suspension, USP is not administered inadvertently to a pregnant woman, it is important that the first injection be given only during the first 5 days after the onset of a normal menstrual period within 5 days postpartum if not breast-feeding and if breast-feeding, at the sixth week postpartum (see DOSAGE AND ADMINISTRATION).

7. Ectopic Pregnancy

Health-care providers should be alert to the possibility of an ectopic pregnancy among women using Medroxyprogesterone Acetate Injectable Suspension, USP who become pregnant or complain of severe abdominal pain.

8. Lactation

Detectable amounts of drug have been identified in the milk of mothers receiving Medroxyprogesterone Acetate Injectable Suspension, USP. In nursing mothers treated with Medroxyprogesterone Acetate Injectable Suspension, USP, milk composition, quality, and amount are not adversely affected. Neonates and infants exposed to medroxyprogesterone from breast milk have been studied for developmental and behavioral effects through puberty. No adverse effects have been noted.

9. Anaphylaxis and Anaphylactoid Reaction

Anaphylaxis and anaphylactoid reaction have been reported with the use of Medroxyprogesterone Acetate Injectable Suspension, USP. If an anaphylactic reaction occurs appropriate therapy should be instituted. Serious anaphylactic reactions require emergency medical treatment.

PRECAUTIONS

GENERAL

1. Physical Examination

It is good medical practice for all women to have annual history and physical examinations, including women using Medroxyprogesterone Acetate Injectable Suspension, USP. The physical examination, however, may be deferred until after initiation of Medroxyprogesterone Acetate Injectable Suspension, USP if requested by the woman and judged appropriate by the clinician. The physical examination should include special reference to blood pressure, breasts, abdomen and pelvic organs, including cervical cytology and relevant laboratory tests. In case of undiagnosed, persistent or recurrent abnormal vaginal bleeding, appropriate measures should be conducted to rule out malignancy. Women with a strong family history of breast cancer or who have breast nodules should be monitored with particular care.

2. Fluid Retention

Because progestational drugs may cause some degree of fluid retention, conditions that might be influenced by this condition, such as epilepsy, migraine, asthma, and cardiac or renal dysfunction, require careful observation.

3. Weight Changes

There is a tendency for women to gain weight while on therapy with Medroxyprogesterone Acetate Injectable Suspension, USP. From an initial average body weight of 136 lb, women who completed 1 year of therapy with Medroxyprogesterone Acetate Injectable Suspension, USP gained an average of 5.4 lb. Women who completed 2 years of therapy gained an average of 8.1 lb.

Women who completed 4 years gained an average of 13.8 lb. Women who completed 6 years gained an average of 16.5 lb. Two percent of women withdrew from a large-scale clinical trial because of excessive weight gain.

4. Return of Fertility

Medroxyprogesterone Acetate Injectable Suspension, USP has a prolonged contraceptive effect. In a large US study of women who discontinued use of Medroxyprogesterone Acetate Injectable Suspension, USP to become pregnant, data are available for 61% of them. Based on Life-Table analysis of these data, it is expected that 68% of women who do become pregnant may conceive within 12 months, 83% may conceive within 15 months, and 93% may conceive within 18 months from the last injection. The median time to conception for those who do conceive is 10 months following the last injection with a range of 4 to 31 months, and is unrelated to the duration of use. No data are available for 39% of the patients who discontinued Medroxyprogesterone Acetate Injectable Suspension, USP to become pregnant and who were lost to follow-up or changed their mind.

5. CNS Disorders and Convulsions

Patients who have a history of psychic depression should be carefully observed and the drug not be readministered if the depression recurs.

There have been a few reported cases of convulsions in patients who were treated with Medroxyprogesterone Acetate Injectable Suspension, USP. Association with drug use or pre-existing conditions is not clear.

6. Carbohydrate Metabolism

A decrease in glucose tolerance has been observed in some patients on Medroxyprogesterone Acetate Injectable Suspension, USP treatment. The mechanism of this decrease is obscure. For this reason, diabetic patients should be carefully observed while receiving such therapy.

7. Liver Function

If jaundice develops, consideration should be given to not readministering the drug.

8. Protection Against Sexually Transmitted Diseases

Patients should be counseled that this product does not protect against HIV infection (AIDS) and other sexually transmitted diseases.

DRUG INTERACTIONS

Aminoglutethimide administered concomitantly with the Medroxyprogesterone Acetate Injectable Suspension, USP may significantly depress the serum concentrations of medroxyprogesterone acetate.^12 Users of Medroxyprogesterone Acetate Injectable Suspension, USP should be warned of the possibility of decreased efficacy with the use of this or any related drugs.

LABORATORY TEST INTERACTIONS

The pathologist should be advised of progestin therapy when relevant specimens are submitted.

The following laboratory tests may be affected by progestins including Medroxyprogesterone Acetate Injectable Suspension, USP:

(a) Plasma and urinary steroid levels are decreased (eg, progesterone, estradiol, pregnanediol, testosterone, cortisol).
(b) Gonadotropin levels are decreased.
(c) Sex-hormone-binding-globulin concentrations are decreased.
(d) Protein-bound iodine and butanol extractable protein-bound iodine may increase.
  T3-uptake values may decrease.
(e) Coagulation test values for prothrombin (Factor II), and Factors VII, VIII, IX, and X may increase.
(f) Sulfobromophthalein and other liver function test values may be increased.
(g) The effects of Medroxyprogesterone Acetate on lipid metabolism are inconsistent. Both increases and decreases in total cholesterol, triglycerides, low-density lipoprotein (LDL) cholesterol, and high-density lipoprotein (HDL) cholesterol have been observed in studies.

CARCINOGENESIS

See "WARNINGS" section 3.

PREGNANCY

Pregnancy Category X

See "WARNINGS" section 6.

NURSING MOTHERS

See "WARNINGS" section 8.

PEDIATRIC USE

Medroxyprogesterone Acetate Injectable Suspension, USP is not indicated before menarche. Use of Medroxyprogesterone Acetate Injectable Suspension, USP is associated with significant loss of BMD. This loss of BMD is of particular concern during adolescence and early adulthood, a critical period of bone accretion. In adolescents, interpretation of BMD results should take into account patient age and skeletal maturity. It is unknown if use of Medroxyprogesterone Acetate Injectable Suspension, USP by younger women will reduce peak bone mass and increase the risk of osteoporotic fractures in later life. Other than concerns about loss of BMD, the safety and effectiveness are expected to be the same for postmenarchal adolescents and adult women.

INFORMATION FOR THE PATIENT

See Patient Labeling.

Patient labeling is included with each single-dose vial and prefilled syringe of Medroxyprogesterone Acetate Injectable Suspension, USP to help describe its characteristics to the patient. It is recommended that prospective users be given this labeling and be informed about the risks and benefits associated with the use of Medroxyprogesterone Acetate Injectable Suspension, USP, as compared with other forms of contraception or with no contraception at all. It is recommended that physicians or other health-care providers responsible for those patients advise them at the beginning of treatment that their menstrual cycle may be disrupted and that irregular and unpredictable bleeding or spotting results, and that this usually decreases to the point of amenorrhea as treatment with Medroxyprogesterone Acetate Injectable Suspension, USP continues, without other therapy being required.

ADVERSE REACTIONS

In the largest clinical trial with Medroxyprogesterone Acetate Injectable Suspension, USP, over 3,900 women, who were treated for up to 7 years, reported the following adverse reactions, which may or may not be related to the use of Medroxyprogesterone Acetate Injectable Suspension, USP.

The following adverse reactions were reported by more than 5% of subjects:

Menstrual irregularities (bleeding or amenorrhea, or both)
Abdominal pain or discomfort
Weight changes
Dizziness
Headache
Asthenia (weakness or fatigue)
Nervousness

Adverse reactions reported by 1% to 5% of subjects using Medroxyprogesterone Acetate Injectable Suspension, USP were:

Decreased libido or anorgasmia
Pelvic pain
Backache
Breast pain
Leg cramps
No hair growth or alopecia
Depression
Bloating
Nausea
Rash
Insomnia
Edema
Leukorrhea
Hot flashes
Acne
Arthralgia
Vaginitis

Events reported by fewer than 1% of subjects included: galactorrhea, melasma, chloasma, convulsions, changes in appetite, gastrointestinal disturbances, jaundice, genitourinary infections, vaginal cysts, dyspareunia, paresthesia, chest pain, pulmonary embolus, allergic reactions, anemia, drowsiness, syncope, dyspnea and asthma, tachycardia, fever, excessive sweating and body odor, dry skin, chills, increased libido, excessive thirst, hoarseness, pain at injection site, blood dyscrasia, rectal bleeding, changes in breast size, breast lumps or nipple bleeding, axillary swelling, breast cancer, prevention of lactation, sensation of pregnancy, lack of return to fertility, paralysis, facial palsy, scleroderma, osteoporosis, uterine hyperplasia, cervical cancer, varicose veins, dysmenorrhea, hirsutism, unexpected pregnancy, thrombophlebitis, deep vein thrombosis.

Postmarketing Experience

There have been rare cases of osteoporosis including osteoporotic fractures reported postmarketing in patients taking Medroxyprogesterone Acetate Injectable Suspension, USP. In addition, there have been voluntary reports of anaphylaxis and anaphylactoid reaction associated with the use of Medroxyprogesterone Acetate Injectable Suspension, USP.

DOSAGE AND ADMINISTRATION

Both the 1 mL vial and the 1 mL prefilled syringe of Medroxyprogesterone Acetate Injectable Suspension, USP should be vigorously shaken just before use to ensure that the dose being administered represents a uniform suspension.

The recommended dose is 150 mg of Medroxyprogesterone Acetate Injectable Suspension, USP every 3 months (13 weeks) administered by deep, IM injection in the gluteal or deltoid muscle. To ensure the patient is not pregnant at the time of the first injection, the first injection MUST be given ONLY during the first 5 days of a normal menstrual period; ONLY within the first 5-days postpartum if not breast-feeding; and if exclusively breast-feeding, ONLY at the sixth postpartum week. If the time interval between injections is greater than 13 weeks, the physician should determine that the patient is not pregnant before administering the drug. The efficacy of depends on adherence to the dosage schedule of a Medroxyprogesterone Acetate Injectable Suspension, USP administration.

HOW SUPPLIED

Medroxyprogesterone Acetate Injectable Suspension, USP (Medroxyprogesterone Acetate sterile aqueous suspension 150 mg/mL) is available as:

1 mL vial NDC 54868-5257-0

Store at controlled room temperature 20° to 25°C (68° to 77°F) [see USP].

REFERENCES

1. Trussell J, Hatcher RA, Cates W Jr, Stewart FH, Kost K. A guide to interpreting contraceptive efficacy studies. Obstet Gynecol. 1990; 76:558–567.
2. Schwallie PC, Assenzo JR. Contraceptive use-efficacy study utilizing Medroxyprogesterone Acetate administered as an intramuscular injection once every 90 days. Fertil Steril. 1973; 24:331–339.
3. WHO Collaborative Study of Neoplasia and Steroid Contraceptives. Breast cancer and depot-medroxyprogesterone acetate: a multi-national study. Lancet. 1991; 338:833–838.
4. WHO Collaborative Study of Neoplasia and Steroid Contraceptives. Depot-Medroxyprogesterone Acetate (DMPA) and risk of epithelial ovarian cancer. Int J Cancer. 1991; 49:191–195.
5. WHO Collaborative Study of Neoplasia and Steroid Contraceptives. Depot-Medroxyprogesterone Acetate (DMPA) and risk of liver cancer. Int J Cancer. 1991; 49:182185.
6. WHO Collaborative Study of Neoplasia and Steroid Contraceptives. Depot-Medroxyprogesterone Acetate (DMPA) and risk of invasive squamous-cell cervical cancer. Contraception. 1992; 45:299–312.
7. WHO Collaborative Study of Neoplasia and Steroid Contraceptives. Depot-Medroxyprogesterone Acetate (DMPA) and risk of endometrial cancer. Int J Cancer. 1991; 49:186–190.
8. Surveillance, Epidemiology, and End Results: Incidence and Mortality Data, 1973–1977. National Cancer Institute Monograph, 57: June 1981. (NIH publication No. 81-2330).
9. Gray RH, Pardthaisong T. In Utero exposure to steroid contraceptives and survival during infancy. Am J Epidemiol. 1991; 134:804–811.
10. Pardthaisong T, Gray RH. In Utero exposure to steroid contraceptives and outcome of pregnancy. Am J Epidemiol. 1991; 134:795–803.
11. Pardthaisong T, Gray RH, McDaniel EB, Chandacham A. Steroid contraceptive use and pregnancy outcome. Teratology. 1988; 38:51–58.
12. Van Deijk WA, Biljham GH, Mellink WAM, Meulenberg PMM. Influence of aminoglutethimide on plasma levels of medroxyprogesterone acetate: its correlation with serum cortisol. Cancer Treatment Reports. 1985; 69:1, 85–90.
13. Paul C, Skegg DCG, Spears GFS. Depot medroxyprogesterone (Depo-Provera) and risk of breast cancer. Br Med J. 1989; 299:759–762.
14. Skegg DCG, Noonan EA, Paul C, Spears GFS, Meirik O, Thomas DB. Depot Medroxyprogesterone Acetate and Breast Cancer: A Pooled Analysis from the World Health Organization and New Zealand Studies. JAMA. 1995; 273(10):799–804.

Rx only

LAB-0150-5.0
June 2008

Relabeling of "Additional" barcode label by:

Physicians Total Care, Inc.
Tulsa, OK 74146

Medroxyprogesterone Acetate Injectable Suspension, USP

Patient Labeling

BOXED WARNING

Use of Medroxyprogesterone Acetate Injectable Suspension, USP may cause you to lose calcium stored in your bones. The longer you use Medroxyprogesterone Acetate Injectable Suspension, USP the more calcium you are likely to lose. The calcium may not return completely once you stop using Medroxyprogesterone Acetate Injectable Suspension, USP.

Loss of calcium may cause weak, porous bones (osteoporosis) that could increase the risk that your bones might break, especially after menopause. It is not known whether your risk of developing osteoporosis may be greater if you are a teenager when you start to use Medroxyprogesterone Acetate Injectable Suspension, USP.

You should use Medroxyprogesterone Acetate Injectable Suspension, USP long term (for example, more than two years) only if other methods of birth control are not right for you. (See "Risks of Using Medroxyprogesterone Acetate Injectable Suspension, USP")

This product is intended to prevent pregnancy. It does not protect against HIV infection (AIDS) and other sexually transmitted diseases.

Introduction

Every woman who considers using Medroxyprogesterone Acetate Injectable Suspension, USP needs to understand the benefits and risks of this form of birth control and to discuss them with her health-care provider. This leaflet is intended to give you much of the information you will need in order to decide if Medroxyprogesterone Acetate Injectable Suspension, USP is the right choice for you. Your health-care provider will help you to compare Medroxyprogesterone Acetate Injectable Suspension, USP with other contraceptive methods and will answer any questions you have after you have read this information.

Medroxyprogesterone Acetate Injectable Suspension, USP is given as an intramuscular injection (a shot) in the buttock or upper arm once every 3 months (13 weeks). Promptly at the end of the 3-month interval, you will need to return to your health-care provider for your next injection in order to continue your contraceptive protection.

Medroxyprogesterone Acetate Injectable Suspension, USP contains medroxyprogesterone acetate, a chemical similar to (but not the same as) the natural hormone progesterone that is produced by your ovaries during the second half of your menstrual cycle. Medroxyprogesterone Acetate Injectable Suspension, USP acts by preventing your egg cells from ripening. If an egg is not released from the ovaries during your menstrual cycle, it cannot become fertilized by sperm and result in pregnancy. Medroxyprogesterone Acetate Injectable Suspension, USP also causes changes in the lining of your uterus that make it less likely for pregnancy to occur.

Effectiveness of Medroxyprogesterone Acetate Injectable Suspension, USP

To ensure that Medroxyprogesterone Acetate Injectable Suspension, USP is not administered inadvertently to a pregnant woman, the first injection must be given ONLY during the first 5 days of a normal menstrual period; ONLY within the first 5-days postpartum if not breast-feeding, and if exclusively breast-feeding, ONLY at the sixth postpartum week (see Administration of Medroxyprogesterone Acetate Injectable Suspension, USP). The efficacy of Medroxyprogesterone Acetate Injectable Suspension, USP depends on adherence to the recommended dosage schedule.

Medroxyprogesterone Acetate Injectable Suspension, USP is over 99% effective, making it one of the most reliable methods of birth control available. This means that the average annual pregnancy rate is less than one for every 100 women who use Medroxyprogesterone Acetate Injectable Suspension, USP. The effectiveness of most contraceptive methods depends, in part, on how reliably each woman uses the method. The effectiveness of Medroxyprogesterone Acetate Injectable Suspension, USP depends only on the patient returning every 3 months (13 weeks) for her next injection.

The following table shows the percent of women who become pregnant while using different kinds of contraceptive methods. It gives both the lowest expected rate of pregnancy (the rate expected in women who use each method exactly as it should be used) and the typical rate of pregnancy (which includes women who became pregnant because they forgot to use their birth control or because they did not follow the directions exactly).

Percent of Women Experiencing an Accidental Pregnancy in the First Year of Continuous Use
Method | Lowest | Typical
Medroxyprogesterone Acetate | 0.3 | 0.3
Implants (Norplant) | 0.2 [From Norplant® package insert.] | 0.2
Female sterilization | 0.2 | 0.4
Male sterilization | 0.1 | 0.15
Oral contraceptives (pill) | — | 3
Combined | 0.1 | —
Progestogen only | 0.5 | —
IUD | — | 3
Progestasert | 2 | —
Copper T 380A | 0.8 | —
Condom (without spermicide) | 2 | 12
Diaphragm (with spermicide) | 6 | 18
Cervical cap | 6 | 18
Withdrawal | 4 | 18
Periodic abstinence | 1–9 | 20
Spermicide alone | 3 | 21
Vaginal sponge | — | —
used before childbirth | 6 | 18
used after childbirth | 9 | 28
No method | 85 | 85
Source: Trussell et al; Obstet Gynecol 1990;76:558–567.

Who Should Not Use Medroxyprogesterone Acetate Injectable Suspension, USP

Certain women should not use Medroxyprogesterone Acetate Injectable Suspension, USP. You should not use Medroxyprogesterone Acetate Injectable Suspension, USP if you have any of the following conditions:

- if you think you might be pregnant
- if you have any vaginal bleeding without a known reason
- if you have had cancer of the breast
- if you have had a stroke
- if you have or have had blood clots (phlebitis) in your legs
- if you have problems with your liver or liver disease
- if you are allergic to Medroxyprogesterone Acetate Injectable Suspension, USP (medroxyprogesterone acetate or any of its other ingredients)

Other Things to Consider Before Choosing Medroxyprogesterone Acetate Injectable Suspension, USP

Before your doctor prescribes Medroxyprogesterone Acetate Injectable Suspension, USP, you will have a physical examination. It is important to tell your doctor or health-care provider if you have any of the following:

- a family history of cancer of the breast
- an abnormal mammogram (breast X-ray), fibrocystic breast disease, breast nodules or lumps, or bleeding from your nipples
- kidney disease
- irregular or scanty menstrual periods
- high blood pressure
- migraine headaches
- asthma
- epilepsy (convulsions or seizures)
- diabetes or a family history of diabetes
- a history of depression
- if you are taking any prescription or over-the-counter medications

This product is intended to prevent pregnancy. It does not protect against transmission of HIV (AIDS) and other sexually transmitted diseases such as chlamydia, genital herpes, genital warts, gonorrhea, hepatitis B, and syphilis.

Return of Fertility

Because Medroxyprogesterone Acetate Injectable Suspension, USP is a long-acting birth control method, it takes some time after your last injection for its effect to wear off. Based on the results from a large study done in the United States, of those women who stop using Medroxyprogesterone Acetate Injectable Suspension, USP in order to become pregnant, about half of those who become pregnant do so in about 10 months after their last injection; about two-thirds of those who become pregnant do so in about 12 months, about 83% of those who become pregnant do so in about 15 months, and about 93% of those who become pregnant do so in about 18 months after their last injection. The length of time you use Medroxyprogesterone Acetate Injectable Suspension, USP has no effect on how long it takes you to become pregnant after you stop using it.

Risks of Using Medroxyprogesterone Acetate Injectable Suspension, USP

1. Losing Calcium from Your Bones

Medroxyprogesterone Acetate Injectable Suspension, USP use may decrease the amount of calcium in your bones. The longer you are on Medroxyprogesterone Acetate Injectable Suspension, USP the more calcium you may lose. This increases the risk of your bones weakening if you use Medroxyprogesterone Acetate Injectable Suspension, USP continuously for a long time (for more than 2 years). The loss of calcium may increase your risk of osteoporosis and broken bones, particularly after your menopause.

Calcium is generally added to the bones during teenage years. The decrease of calcium in your bones is of most concern if you are a teenager or have the following risk factors:

- bone disease
- anorexia nervosa (an eating disorder)
- a strong family history of osteoporosis
- drug use that can lower the amount of calcium in bones (drugs for epilepsy or steroids), or
- drinking a lot of alcohol or smoking a lot.

If you need a birth control method for more than 2 years, your healthcare provider may ask you to switch to another birth control method or ask you to have a test of your bones before continuing Medroxyprogesterone Acetate Injectable Suspension, USP, especially if you have other risks for weak bones. When Medroxyprogesterone Acetate Injectable Suspension, USP is stopped, the calcium in bones begins to come back. Your healthcare provider may tell you take calcium and Vitamin D as this may lessen the loss of calcium from your bones.

2. Irregular Menstrual Bleeding

The side effect reported most frequently by women who use Medroxyprogesterone Acetate Injectable Suspension, USP for contraception is a change in their normal menstrual cycle. During the first year of using Medroxyprogesterone Acetate Injectable Suspension, USP, you might have one or more of the following changes:

- irregular or unpredictable bleeding or spotting,
- an increase or decrease in menstrual bleeding, or
- no bleeding at all.

Unusually heavy or continuous bleeding, however, is not a usual effect of Medroxyprogesterone Acetate Injectable Suspension, USP and if this happens you should see your health-care provider right away.

With continued use of Medroxyprogesterone Acetate Injectable Suspension, USP, bleeding usually decreases and many women stop having periods completely. In clinical studies of Medroxyprogesterone Acetate Injectable Suspension, USP, 55% of the women studied reported no menstrual bleeding (amenorrhea) after 1 year of use and 68% of the women studied reported no menstrual bleeding after 2 years of use.

The reason that your periods stop is because Medroxyprogesterone Acetate Injectable Suspension, USP causes a resting state in your ovaries. When your ovaries do not release an egg monthly, the regular monthly growth of the lining of your uterus does not occur and, therefore, the bleeding that comes with your normal menstruation does not take place. When you stop using Medroxyprogesterone Acetate Injectable Suspension, USP your menstrual period will usually, in time, return to its normal cycle.

3. Cancer

Studies of women who have used different forms of contraception found that women who used Medroxyprogesterone Acetate Injectable Suspension, USP for contraception had no increased overall risk of developing cancer of the breast, ovary, uterus, cervix, or liver. However, women under 35 years of age whose first exposure to Medroxyprogesterone Acetate Injectable Suspension, USP was within the previous 4 to 5 years may have a slightly increased risk of developing breast cancer similar to that seen with oral contraceptives. You should discuss this with your health-care provider.

4. Unexpected Pregnancy

Because Medroxyprogesterone Acetate Injectable Suspension, USP is such an effective contraceptive method, the risk of unexpected pregnancy for women who get their shots regularly (every 3 months [13 weeks]) is very low. While there have been reports of an increased risk of low birth weight and neonatal infant death or other health problems in infants conceived close to the time of injection, such pregnancies are uncommon. If you think you may have become pregnant while using Medroxyprogesterone Acetate Injectable Suspension, USP for contraception, see your health-care provider as soon as possible.

5. Allergic Reactions

Severe allergic reactions known as anaphylaxis and anaphylactoid reactions have also been reported in some women using Medroxyprogesterone Acetate Injectable Suspension, USP.

6. Other Risks

Women who use hormone-based contraceptives may have an increased risk of blood clots or stroke. Also, if a contraceptive method fails, there is a possibility that the fertilized egg will begin to develop outside of the uterus (ectopic pregnancy). While these events are rare, you should tell your health-care provider if you have any of the Warning Signals listed in the next section.

Warning Signals

If any of these problems occur following an injection of Medroxyprogesterone Acetate Injectable Suspension, USP, call your healthcare provider immediately:

- Sharp chest pain, coughing up of blood, or sudden shortness of breath (indicating a possible clot in the lung)
- Sudden severe headache or vomiting, dizziness or fainting, problems with your eyesight or speech, weakness, or numbness in an arm or leg (indicating a possible stroke)
- Severe pain or swelling in the calf (indicating a possible clot in the leg)
- Unusually heavy vaginal bleeding
- Severe pain or tenderness in the lower abdominal area
- Persistent pain, pus, or bleeding at the injection site

Side Effects of Medroxyprogesterone Acetate Injectable Suspension, USP

1. Weight Gain

You may experience a weight gain while you are using Medroxyprogesterone Acetate Injectable Suspension, USP. About two-thirds of the women who used Medroxyprogesterone Acetate Injectable Suspension, USP in the clinical trials reported a weight gain of about 5 pounds during the first year of use. You may continue to gain weight after the first year. Women in one large study who used Medroxyprogesterone Acetate Injectable Suspension, USP for 2 years gained an average total of 8.1 pounds over those 2 years, or approximately 4 pounds per year. Women who continued for 4 years gained an average total of 13.8 pounds over those 4 years, or approximately 3.5 pounds per year. Women who continued for 6 years gained an average total of 16.5 pounds over those 6 years, or approximately 2.75 pounds per year.

2. Other Side Effects

In a clinical study of over 3,900 women who used Medroxyprogesterone Acetate Injectable Suspension, USP for up to 7 years, some women reported the following effects that may or may not have been related to their use of Medroxyprogesterone Acetate Injectable Suspension, USP:

• irregular menstrual bleeding

• swelling of the hands or feet

• amenorrhea

• backache

• headache

• depression

• nervousness

• insomnia

• abdominal cramps

• acne

• dizziness

• pelvic pain

• weakness or fatigue

• no hair growth or excessive hair loss

• decreased sexual desire

• rash

• leg cramps

• hot flashes

• nausea

• joint pain

• vaginal discharge or irritation

• breast swelling and tenderness

• bloating

Other problems were reported by very few of the women in the clinical trials, but some of these could be serious. These include: convulsions, jaundice, urinary tract infections, allergic reactions, fainting, paralysis, osteoporosis, lack of return to fertility, deep vein thrombosis, pulmonary embolus, breast cancer, or cervical cancer. If these or any other problems occur during your use of Medroxyprogesterone Acetate Injectable Suspension, USP, discuss them with your health-care provider.

General Precautions

1. Missed Periods

During the time you are using Medroxyprogesterone Acetate Injectable Suspension, USP for contraception, you may skip a period, or your periods may stop completely. If you have been receiving your injection of Medroxyprogesterone Acetate Injectable Suspension, USP regularly every 3 months (13 weeks), then you are probably not pregnant. However, if you think that you may be pregnant, see your health-care provider.

2. Laboratory Test Interactions

If you are scheduled for any laboratory tests, tell your health-care provider that you are using Medroxyprogesterone Acetate Injectable Suspension, USP for contraception. Certain blood tests are affected by hormones such as Medroxyprogesterone Acetate Injectable Suspension, USP.

3. Drug Interactions

Cytadren (aminoglutethimide) is an anticancer drug that may significantly decrease the effectiveness of Medroxyprogesterone Acetate Injectable Suspension, USP if the two drugs are given during the same time.

4. Nursing Mothers

Although Medroxyprogesterone Acetate Injectable Suspension, USP can be passed to the nursing infant in the breast milk, no harmful effects have been found in these children. Medroxyprogesterone Acetate Injectable Suspension, USP does not prevent the breasts from producing milk, so it can be used by nursing mothers. However, to minimize the amount of Medroxyprogesterone Acetate Injectable Suspension, USP that is passed to the infant in the first weeks after birth, you should wait until 6 weeks after childbirth before you start using Medroxyprogesterone Acetate Injectable Suspension, USP for contraception.

Administration of Medroxyprogesterone Acetate Injectable Suspension, USP

The recommended dose of Medroxyprogesterone Acetate Injectable Suspension, USP is 150 mg every 3 months (13 weeks) given in a single intramuscular injection in the buttock or upper arm. To ensure that you are not pregnant at the time of the first injection, it is essential that the injection be given ONLY during the first 5 days of a normal menstrual period. If used following the delivery of a child, the first injection of Medroxyprogesterone Acetate Injectable Suspension, USP MUST be given within 5 days after childbirth if you are not breast-feeding, or if you are exclusively breast-feeding, the injection MUST be given 6 weeks after childbirth. If you wait longer than 3 months (13 weeks) between injections, or longer than 6 weeks after delivery, your health-care provider should determine that you are not pregnant before giving you your injection of Medroxyprogesterone Acetate Injectable Suspension, USP.

Rx only

LAB-0152-5.0
June 2008

PRINCIPAL DISPLAY PANEL - 1 mL Vial

NDC 54868-5257-0

medroxyprogesterone
acetate injectable
suspension, USP

150 mg in 1 mL

Intramuscular Use Only